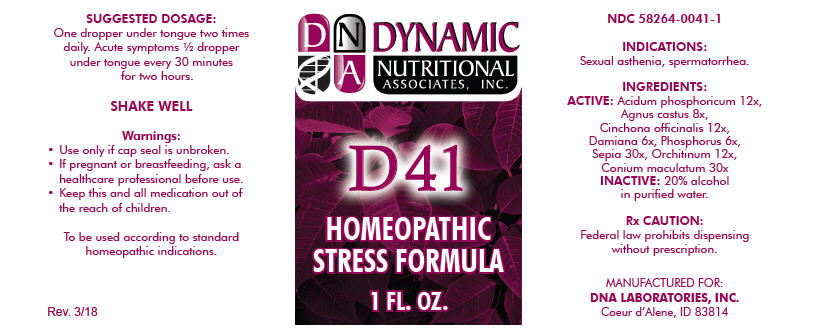 DRUG LABEL: D-41
NDC: 58264-0041 | Form: SOLUTION
Manufacturer: DNA Labs, Inc.
Category: homeopathic | Type: HUMAN OTC DRUG LABEL
Date: 20250113

ACTIVE INGREDIENTS: PHOSPHORIC ACID 12 [hp_X]/1 mL; CHASTE TREE 8 [hp_X]/1 mL; CINCHONA OFFICINALIS BARK 12 [hp_X]/1 mL; TURNERA DIFFUSA LEAFY TWIG 6 [hp_X]/1 mL; PHOSPHORUS 6 [hp_X]/1 mL; SEPIA OFFICINALIS JUICE 30 [hp_X]/1 mL; BOS TAURUS TESTICLE 12 [hp_X]/1 mL; CONIUM MACULATUM FLOWERING TOP 30 [hp_X]/1 mL
INACTIVE INGREDIENTS: ALCOHOL; WATER

D-41

NDC 58264-0041-1

INDICATIONS

PURPOSE

Sexual asthenia, spermatorrhea.

INGREDIENTS

ACTIVE

Acidum phosphoricum 12x, Agnus castus 8x, Cinchona officinalis 12x, Damiana 6x, Phosphorus 6x, Sepia 30x, Orchitinum 12x, Conium maculatum 30x

INACTIVE

20% alcohol in purified water.

Rx CAUTION

Federal law prohibits dispensing without prescription.

SUGGESTED DOSAGE

One dropper under tongue two times daily. Acute symptoms ½ dropper under tongue every 30 minutes for two hours.

STORAGE AND HANDLING

SHAKE WELL

Warnings

- Use only if cap seal is unbroken.

PREGNANCY OR BREAST FEEDING

- If pregnant or breastfeeding, ask a healthcare professional before use.

KEEP OUT OF REACH OF CHILDREN

- Keep this and all medication out of the reach of children.

To be used according to standard homeopathic indications.

PRINCIPAL DISPLAY PANEL - 1 FL. OZ. Bottle Label

DYNAMIC
NUTRITIONAL
ASSOCIATES, INC.

D 41

HOMEOPATHIC
STRESS FORMULA

1 FL. OZ.